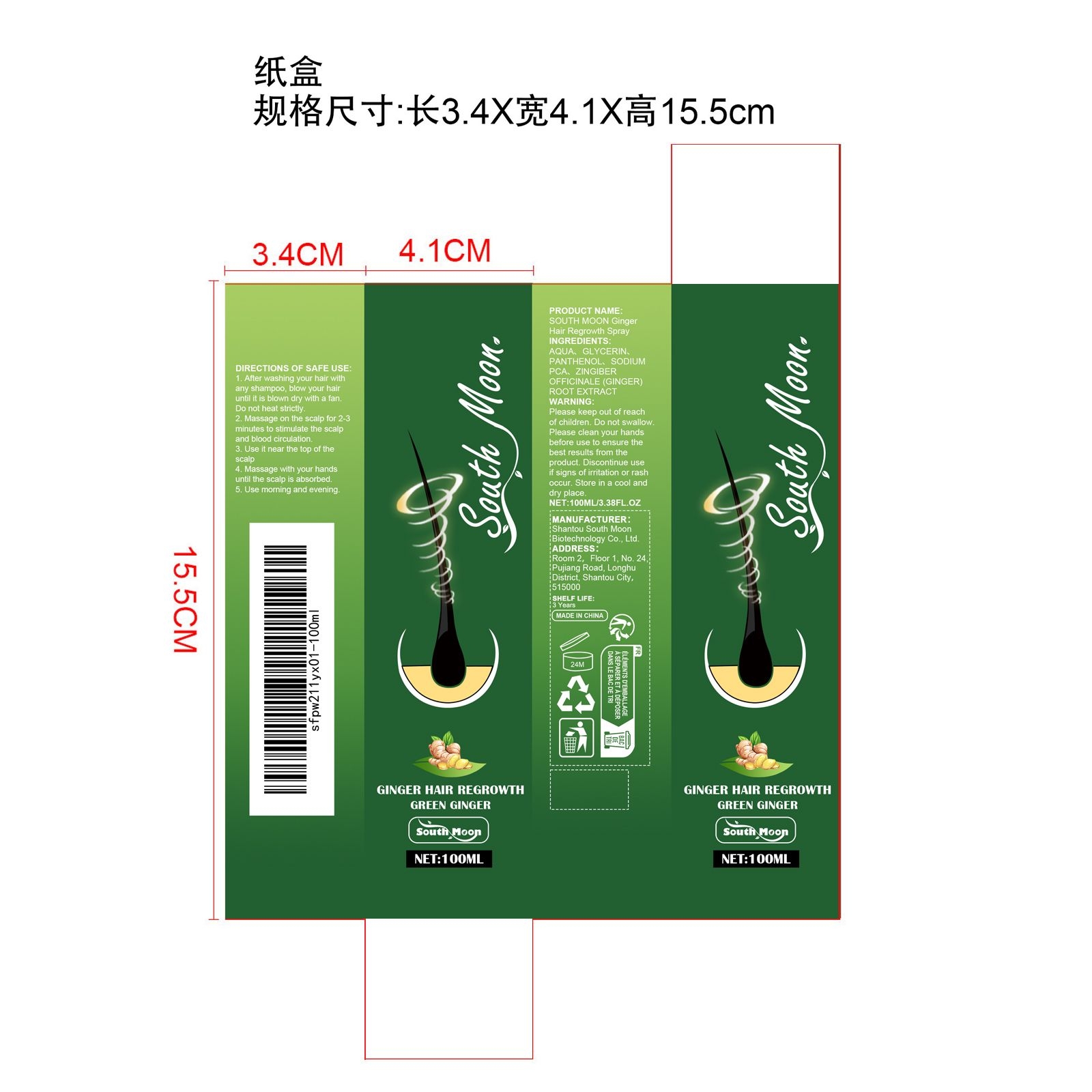 DRUG LABEL: SOUTH MOON Ginger Hair Regrowth
NDC: 84983-009 | Form: LIQUID
Manufacturer: Shantou South Moon Biotechnology Co., Ltd.
Category: otc | Type: HUMAN OTC DRUG LABEL
Date: 20251127

ACTIVE INGREDIENTS: ZINGIBER OFFICINALE (GINGER) ROOT OIL 0.02 mg/100 mg
INACTIVE INGREDIENTS: AQUA 93.48 mg/100 mg; GLYCERIN 4 mg/100 mg; PANTHENOL 1.5 mg/100 mg; SODIUM PCA 1 mg/100 mg

ACTIVE INGREDIENT

ZINGIBER OFFICINALE (GINGER) ROOT OIL

WHEN USING

1. After washing your hair with any shampoo, blow your hair until it is blown dry with a fan. Do not heat strictly.

2. Massage on the scalp for 2-3 minutes to stimulate the scalp and blood circulation.

3. Use it near the top of the scalp

4. Massage with your hands until the scalp is absorbed.

5. Use morning and evening.

PURPOSE

/

WARNINGS

Please keep out of reach of children. Do not swallow.Please clean your hands before use to ensure the best results from the product. Discontinue use if signs of irritation or rash occur. Store in a cool and dry place.

KEEP OUT OF REACH OF CHILDREN

Please keep out of reach of children. Do not swallow.

STOP USE

Discontinue use if signs of irritation or rash occur.

DO NOT USE

Discontinue use if signs of irritation or rash occur.

STORAGE AND HANDLING

Store in a cool and dry place.

INACTIVE INGREDIENT

AQUA、GLYCERIN、PANTHENOL、SODIUM PCA